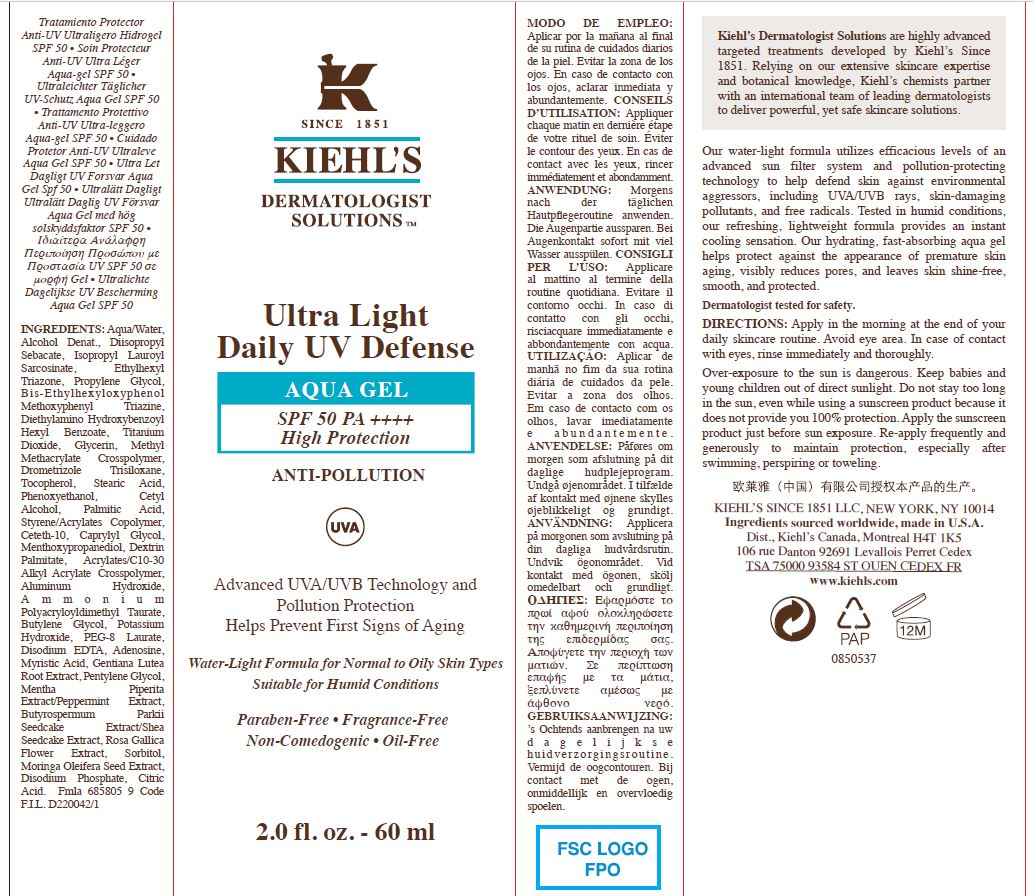 DRUG LABEL: Kiehls Ultra Light Daily UV Defense Aqua Gel SPF 50 Anti-Pollution
NDC: 49967-455 | Form: GEL
Manufacturer: L'Oreal USA Products Inc.
Category: otc | Type: HUMAN OTC DRUG LABEL
Date: 20240130

ACTIVE INGREDIENTS: Ethylhexyl triazone 50 mg/1 mL; Diethylamino hydroxybenzoyl hexyl benzoate 30 mg/1 mL; BEMOTRIZINOL 30 mg/1 mL; DROMETRIZOLE TRISILOXANE 10 mg/1 mL; TITANIUM DIOXIDE 25 mg/1 mL
INACTIVE INGREDIENTS: WATER; ALCOHOL; DIISOPROPYL SEBACATE; ISOPROPYL LAUROYL SARCOSINATE; PROPYLENE GLYCOL; GLYCERIN; METHYL METHACRYLATE/GLYCOL DIMETHACRYLATE CROSSPOLYMER; TOCOPHEROL; STEARIC ACID; PHENOXYETHANOL; CETYL ALCOHOL; PALMITIC ACID; STYRENE/ACRYLAMIDE COPOLYMER (500000 MW); CETETH-10; CAPRYLYL GLYCOL; 3-((L-MENTHYL)OXY)PROPANE-1,2-DIOL; DEXTRIN PALMITATE (CORN; 20000 MW); ALUMINUM HYDROXIDE; AMMONIUM POLYACRYLOYLDIMETHYL TAURATE (55000 MPA.S); BUTYLENE GLYCOL; POTASSIUM HYDROXIDE; PEG-8 LAURATE; EDETATE DISODIUM ANHYDROUS; ADENOSINE; MYRISTIC ACID; GENTIANA LUTEA ROOT; PENTYLENE GLYCOL; MENTHA PIPERITA; SHEANUT; ROSA GALLICA FLOWER; SORBITOL; MORINGA OLEIFERA SEED; SODIUM PHOSPHATE, DIBASIC, ANHYDROUS; CITRIC ACID MONOHYDRATE

Drug Facts

Directions

Apply in the morning at the end of your daily skincare routine. Avoid eye area. In case of contact with eyes, rinse immediately and thoroughly.

Over-exposure to the sun in dangerous. Keep babies and young children out of direct sunlight. Do not stay too long in the sun, even while using a sunscreen product because it does not provide you 100% protection. Apply the sunscreen product just before sun exposure. Re-apply frequently and generously to maintain protection, especially after swimming, perspiring or toweling.